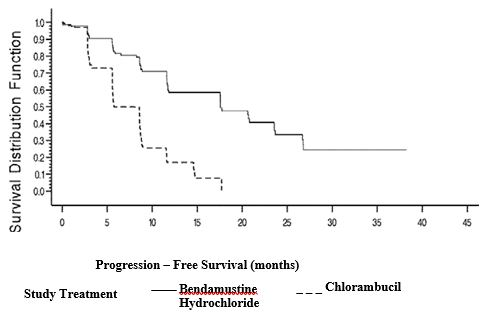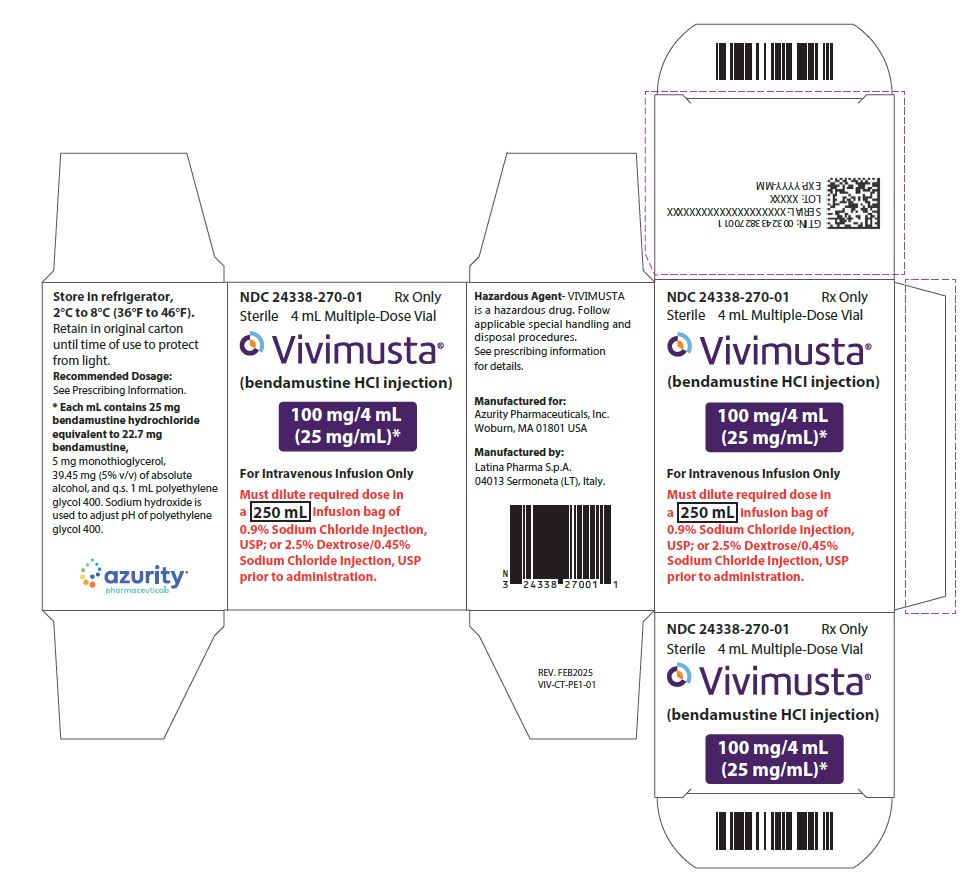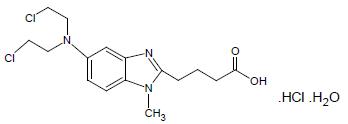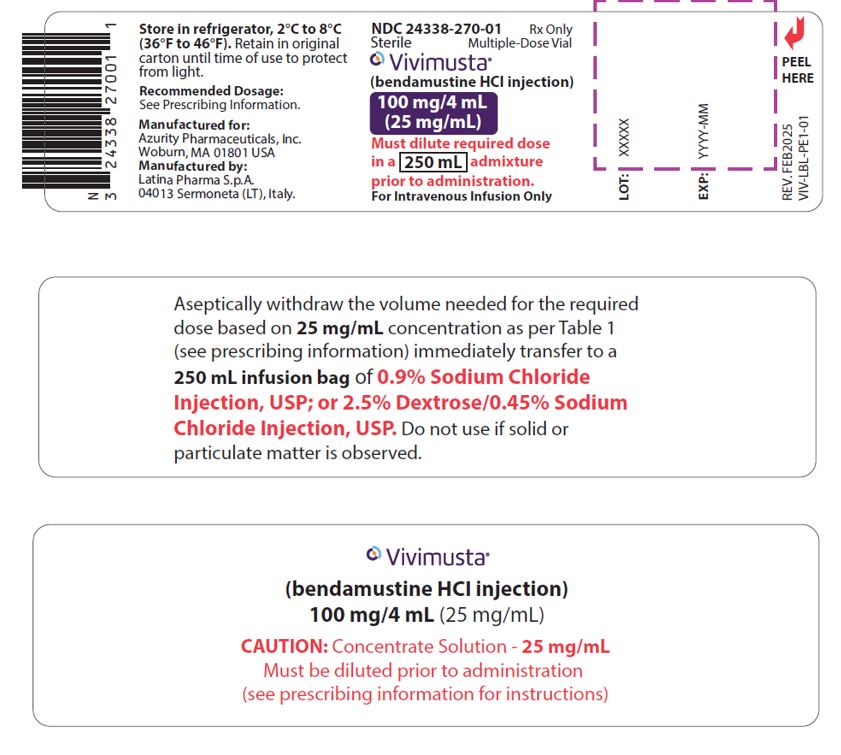 DRUG LABEL: VIVIMUSTA
NDC: 24338-270 | Form: INJECTION
Manufacturer: Azurity Pharmaceuticals, Inc.
Category: prescription | Type: Human Prescription Drug Label
Date: 20250403

ACTIVE INGREDIENTS: BENDAMUSTINE HYDROCHLORIDE 25 mg/1 mL
INACTIVE INGREDIENTS: MONOTHIOGLYCEROL; POLYETHYLENE GLYCOL 400; SODIUM HYDROXIDE; ALCOHOL

HIGHLIGHTS OF PRESCRIBING INFORMATION

These highlights do not include all the information needed to use VIVIMUSTA safely and effectively. See full prescribing information for VIVIMUSTA.
VIVIMUSTA® (bendamustine hydrochloride injection), for intravenous use.
Initial U.S. Approval: 2008

1 INDICATIONS & USAGE

VIVIMUSTA is an alkylating drug indicated for treatment of patients with:
• Chronic lymphocytic leukemia (CLL). Efficacy relative to first line therapies other than chlorambucil has not been established. (1.1)
• Indolent B-cell non-Hodgkin lymphoma (NHL) that has progressed during or within six months of treatment with rituximab or a rituximab-containing regimen. (1.2)

2 DOSAGE & ADMINISTRATION

For CLL:
• 100 mg/m^2 infused intravenously over 20 minutes on Days 1 and 2 of a 28 day cycle, up to 6 cycles (2.1)

For NHL:
• 120 mg/m^2 infused intravenously over 20 minutes on Days 1 and 2 of a 21 day cycle, up to 8 cycles (2.2)

3 DOSAGE FORMS & STRENGTHS

Injection: 100 mg/4 mL (25 mg/mL) in a multiple-dose vial (3).

4 CONTRAINDICATIONS

History of a hypersensitivity reaction to bendamustine, polyethylene glycol 400, dehydrated alcohol, or monothioglycerol. Reactions to bendamustine hydrochloride have included anaphylaxis and anaphylactoid reactions. (4, 5.4)

5 WARNINGS AND PRECAUTIONS

• Myelosuppression: Delay or reduce dose, and restart treatment based on ANC and platelet count recovery. (5.1)
• Infections: Monitor for fever and other signs of infection or reactivation of infections and treat promptly. (5.2)

• Progressive multifocal leukoencephalopathy (PML): Monitor for new or worsening neurological, cognitive or behavioral signs or symptoms suggestive of PML. (5.3)
• Anaphylaxis and Infusion-Related Reactions: Severe anaphylactic reactions have occurred. Monitor clinically and discontinue drug for severe reactions. Pre-medicate in subsequent cycles for milder reactions. (5.4)
• Tumor Lysis Syndrome: May lead to acute renal failure and death; anticipate and use supportive measures in patients at high risk. (5.5)
• Skin Reactions: Discontinue for severe skin reactions. Cases of SJS, DRESS and TEN, some fatal, have been reported. (5.6).
• Hepatotoxicity: Monitor liver chemistry tests prior to and during treatment. (5.7)
• Other Malignancies: Pre-malignant and malignant diseases have been reported. (5.8)
• Extravasation Injury: Take precautions to avoid extravasation, including monitoring intravenous infusion site during and after administration. (5.9)
• Embryo-Fetal Toxicity: Can cause fetal harm. Advise females of reproductive potential and males with female partners of reproductive potential of the potential risk to a fetus and to use an effective method of contraception. (5.10,8.1, 8.3)

6 ADVERSE REACTIONS

• Adverse reactions (> 5%) during infusion and within 24 hours post-infusion are nausea, and fatigue. (6.1)
• Most common adverse reactions (≥15%) for CLL are anemia, thrombocytopenia, neutropenia, lymphopenia, leukopenia, hyperbilirubinemia, pyrexia, nausea, vomiting. (6.1)
• Most common adverse reactions (≥15%) for NHL are lymphopenia, leukopenia, anemia neutropenia, thrombocytopenia, nausea, fatigue, vomiting, diarrhea, pyrexia, constipation, anorexia, cough, headache, weight decreased dyspnea, rash, and stomatitis. (6.1)
To report SUSPECTED ADVERSE REACTIONS, contact Azurity Pharmaceuticals, Inc. at 1-800-461-7449 or FDA at 1-800-FDA-1088 or www.fda.gov/medwatch

7 DRUG INTERACTIONS

Consider alternative therapies that are not CYP1A2 inducers or inhibitors during treatment with VIVIMUSTA. (7.1)

8 USE IN SPECIFIC POPULATIONS

• Lactation: Advise not to breastfeed. (8.2)
• Infertility: May impair fertility. (8.3)
• Renal Impairment: Do not use in patients with creatinine clearance < 30 mL/min. (8.6)
• Hepatic Impairment: Do not use in patients with total bilirubin 1.5-3 x ULN and AST or ALT 2.5-1.0 x ULN, or total bilirubin > 3 x ULN. (8.7)

FULL PRESCRIBING INFORMATION

1 INDICATIONS & USAGE

1.1 Chronic Lymphocytic Leukemia (CLL)

VIVIMUSTA is indicated for the treatment of adult patients with chronic lymphocytic leukemia. Efficacy relative to first line therapies other than chlorambucil has not been established.

1.2 Non-Hodgkin Lymphoma (NHL)

VIVIMUSTA is indicated for the treatment of adult patients with indolent B-cell non-Hodgkin lymphoma that has progressed during or within six months of treatment with rituximab or a rituximab-containing regimen.

2 DOSAGE & ADMINISTRATION

2.1 Dosing Instructions for CLL

Recommended Dosage
The recommended dosage is 100 mg/m^2 administered intravenously over 20 minutes on Days 1 and 2 of a 28-day cycle for up to 6 cycles.
Dose Delays, Dose Modifications and Re-initiation of Therapy for CLL
Delay VIVIMUSTA for Grade 4 hematologic toxicity or clinically significant Grade 2 or greater non-hematologic toxicity.
Once non-hematologic toxicity has recovered to less than or equal to Grade 1 and/or the blood counts have improved [Absolute Neutrophil Count (ANC) greater than or equal to 1 x 10^9/L and platelets greater than or equal to 75 x 10^9/L], reinitiate VIVIMUSTA at the discretion of the healthcare provider. In addition, consider dose reduction [see Warnings and Precautions (5.1)]
Dose modifications for hematologic toxicity: for Grade 3 or greater toxicity, reduce the dose to 50 mg/m^2 on Days 1 and 2 of each cycle; if Grade 3 or greater toxicity recurs, reduce the dose to 25 mg/m^2 on Days 1 and 2 of each cycle.
Dose modifications for non-hematologic toxicity: for clinically significant Grade 3 or greater toxicity, reduce the dose to 50 mg/m^2 on Days 1 and 2 of each cycle.
Consider dose re-escalation in subsequent cycles at the discretion of the healthcare provider.

2.2 Dosing Instructions for NHL

Recommended Dosage
The recommended dosage is 120 mg/m^2 administered intravenously over 20 minutes on Days 1 and 2 of a 21-day cycle for up to 8 cycles.

Dose Delays, Dose Modifications and Re-initiation of Therapy for NHL
Delay VIVIMUSTA for Grade 4 hematologic toxicity or clinically significant Grade 2 or greater non-hematologic toxicity.
Once non-hematologic toxicity has recovered to less than or equal to Grade 1 and/or the blood counts have improved [Absolute Neutrophil Count (ANC) greater than or equal to 1 x 10^9/L and platelets greater than or equal to 75 x 10^9/L], reinitiate VIVIMUSTA at the discretion of the healthcare provider. In addition, consider dose reduction [see Warnings and Precautions (5.1)]
Dose modifications for hematologic toxicity: for Grade 4 toxicity, reduce the dose to 90 mg/m^2 on Days 1 and 2 of each cycle; if Grade 4 toxicity recurs, reduce the dose to 60 mg/m^2 on Days 1 and 2 of each cycle.
Dose modifications for non-hematologic toxicity: for Grade 3 or greater toxicity, reduce the dose to 90 mg/m^2 on Days 1 and 2 of each cycle; if Grade 3 or greater toxicity recurs, reduce the dose to 60 mg/m^2 on Days 1 and 2 of each cycle.

2.3 Preparation and Administration

VIVIMUSTA is a hazardous drug. Follow applicable special handling and disposal procedures.^1
VIVIMUSTA is a clear and colorless to yellow solution in a multiple-dose vial.

Store VIVIMUSTA refrigerated at 2°C to 8°C (36°F to 46°F). When refrigerated, the contents may partially freeze. Allow the vial to reach room temperature (15°C to 30°C or 59°F to 86°F) prior to use. Observe the contents of the vial for any visible solid or particulate matter. Do not use the product if solid or particulate matter is observed after reaching room temperature.

Intravenous Infusion

Aseptically withdraw the volume needed for the required dose from the 25 mg/mL solution as per Table 1 below and immediately transfer to a 250 mL infusion bag of one of the following diluents: 0.9% Sodium Chloride Injection, USP; or 2.5% Dextrose/0.45% Sodium Chloride Injection, USP.

The resulting final concentration of bendamustine hydrochloride in the infusion bag should be within 0.1 mg/mL to 1.36 mg/mL.
After transferring, thoroughly mix the contents of the infusion bag. The admixture should be a clear and colorless to slightly yellow solution.

No other diluents have been shown to be compatible [see Dosage and Administration (2.4)].

Table 1: Volume of VIVIMUSTA required for Dilution into 250 mL of 0.9% Sodium Chloride Injection, USP, or 2.5% Dextrose/0.45% Sodium Chloride Injection, USP for a Given Dose and Body Surface Area

Body Surface Area (m^2) | Volume of VIVIMUSTA to Withdraw (mL) from Vial
Body Surface Area (m^2) | 120 mg/m^2 | 100 mg/m^2 | 90 mg/m^2 | 60 mg/m^2 | 50 mg/m^2 | 25 mg/m^2
1 | 4.8 | 4 | 3.6 | 2.4 | 2 | 1
1.1 | 5.3 | 4.4 | 4 | 2.6 | 2.2 | 1.1
1.2 | 5.8 | 4.8 | 4.3 | 2.9 | 2.4 | 1.2
1.3 | 6.2 | 5.2 | 4.7 | 3.1 | 2.6 | 1.3
1.4 | 6.7 | 5.6 | 5 | 3.4 | 2.8 | 1.4
1.5 | 7.2 | 6 | 5.4 | 3.6 | 3 | 1.5
1.6 | 7.7 | 6.4 | 5.8 | 3.8 | 3.2 | 1.6
1.7 | 8.2 | 6.8 | 6.1 | 4.1 | 3.4 | 1.7
1.8 | 8.6 | 7.2 | 6.5 | 4.3 | 3.6 | 1.8
1.9 | 9.1 | 7.6 | 6.8 | 4.6 | 3.8 | 1.9
2 | 9.6 | 8 | 7.2 | 4.8 | 4 | 2
2.1 | 10.1 | 8.4 | 7.6 | 5 | 4.2 | 2.1
2.2 | 10.6 | 8.8 | 7.9 | 5.3 | 4.4 | 2.2
2.3 | 11 | 9.2 | 8.3 | 5.5 | 4.6 | 2.3
2.4 | 11.5 | 9.6 | 8.6 | 5.8 | 4.8 | 2.4
2.5 | 12 | 10 | 9 | 6 | 5 | 2.5
2.6 | 12.5 | 10.4 | 9.4 | 6.2 | 5.2 | 2.6
2.7 | 13 | 10.8 | 9.7 | 6.5 | 5.4 | 2.7
2.8 | 13.4 | 11.2 | 10.1 | 6.7 | 5.6 | 2.8
2.9 | 13.9 | 11.6 | 10.4 | 7 | 5.8 | 2.9
3 | 14.4 | 12 | 10.8 | 7.2 | 6 | 3

Parenteral drug products should be inspected visually for particulate matter and discoloration prior to administration whenever solution and container permit. Discard any unused solution according to institutional procedures for hazardous drugs.

2.4 Admixture Stability

VIVIMUSTA contains no antimicrobial preservative. Prepare the admixture as close as possible to the time of patient administration.

Once diluted with 0.9% Sodium Chloride Injection, USP, or 2.5% Dextrose/0.45% Sodium Chloride Injection, USP, the final admixture is stable for 24 hours when stored refrigerated (2°C to 8°C or 36°F to 46°F) or for 3 hours when stored at room temperature (15°C to 30°C or 59°F to 86°F) and room light. Complete administration of diluted VIVIMUSTA within this period of time.
VIVIMUSTA (bendamustine hydrochloride injection) is supplied in a multiple-dose vial. Retain the partially used vial in original package to protect from light and store refrigerated (2°C to 8°C or 36°F to 46°F) if additional dose withdrawal from the same vial is intended.

2.5 Stability of Partially Used Vials (Needle Punched Vials)

VIVIMUSTA is supplied as a multiple-dose vial. Although it does not contain any antimicrobial preservative, VIVIMUSTA is bacteriostatic. The partially used vials are stable for up to 28 days when stored in its original carton under refrigeration (2°C to 8°C or 36°F to 46°F). Each vial is not recommended for more than a total of six (6) dose withdrawals.
After first use, store the partially used vial in the original carton at 2°C to 8°C (36°F to 46°F) and then discard after 28 days.

3 DOSAGE FORMS & STRENGTHS

Injection: 100 mg/4 mL (25 mg/mL) as a clear and colorless to yellow solution in multiple-dose vial.

4 CONTRAINDICATIONS

VIVIMUSTA is contraindicated in patients with a known hypersensitivity (e.g., anaphylactic and anaphylactoid reactions) to bendamustine, polyethylene glycol 400, dehydrated alcohol, or monothioglycerol [see Warnings and Precautions (5.4)]

5 WARNINGS AND PRECAUTIONS

5.1 Myelosuppression

VIVIMUSTA causes myelosuppression. Bendamustine hydrochloride caused severe myelosuppression (Grade 3-4) in 98% of patients in the two NHL studies [see Adverse Reactions (6.1)]. Three patients (2%) died from myelosuppression-related adverse reactions; one each from neutropenic sepsis, diffuse alveolar hemorrhage with Grade 3 thrombocytopenia and pneumonia from an opportunistic infection (CMV).
Monitor complete blood counts, including leukocytes, platelets, hemoglobin (Hgb), and neutrophils frequently. In the clinical trials, blood counts were monitored every week initially. Hematologic nadirs were observed predominantly in the third week of therapy. Myelosuppression may require dose delays and/or subsequent dose reductions if recovery to the recommended values has not occurred by the first day of the next scheduled cycle. Delay the next cycle of therapy if ANC less than 1 x 10^9/L or platelet count less than 75 x 10^9/L [see Dosage and Administration (2.1, 2.2)].

5.2 Infections

Infection, including pneumonia, sepsis, septic shock, hepatitis and death has occurred in adult and pediatric patients in clinical trials and in postmarketing reports for bendamustine hydrochloride [see Adverse Reactions (6.1, 6.2)]. Patients with myelosuppression following treatment with bendamustine hydrochloride are more susceptible to infections. Advise patients with myelosuppression following VIVIMUSTA treatment to contact healthcare provider immediately if they have symptoms or signs of infection.
Patients treated with VIVIMUSTA are at risk for reactivation of infections including (but not limited to) hepatitis B, cytomegalovirus, Mycobacterium tuberculosis, and herpes zoster. Implement appropriate measures (including clinical and laboratory monitoring, prophylaxis, and treatment) for infection and infection reactivation prior to administration.

5.3 Progressive Multifocal Leukoencephalopathy (PML)

Progressive multifocal leukoencephalopathy (PML), including fatal cases, have occurred following treatment with bendamustine, primarily in combination with rituximab or obinutuzumab [see Adverse Reactions (6.2)]. Consider PML in the differential diagnosis in patients with new or worsening neurological, cognitive or behavioral signs or symptoms. If PML is suspected, withhold VIVIMUSTA treatment and perform appropriate diagnostic evaluations. Consider discontinuation or reduction of any concomitant chemotherapy or immunosuppressive therapy in patients who develop PML.

5.4 Anaphylaxis and Infusion-Related Reactions

Infusion-related reactions to bendamustine hydrochloride have occurred commonly in clinical trials. Symptoms include fever, chills, pruritus and rash. In rare instances, severe anaphylactic and anaphylactoid reactions have occurred, particularly in the second and subsequent cycles of therapy.
Monitor clinically and discontinue drug for severe reactions. Ask patients about symptoms suggestive of infusion-related reactions after their first cycle of therapy. Do not rechallenge patients who experienced Grade 3 or worse allergic-type reactions. Consider measures to prevent severe reactions, including antihistamines, antipyretics and corticosteroids in subsequent cycles in patients who have experienced Grade 1 or 2 infusion-related reactions. Discontinue VIVIMUSTA for patients with Grade 4 infusion-related reactions. Consider discontinuation for Grade 3 infusion-related reactions as clinically appropriate considering individual benefits, risks, and supportive care.

5.5 Tumor Lysis Syndrome

Tumor lysis syndrome associated with bendamustine hydrochloride has occurred in patients in clinical trials and in postmarketing reports. The onset tends to be within the first treatment cycle of bendamustine hydrochloride and, without intervention, may lead to acute renal failure and death.
Administer vigorous hydration and monitor blood chemistry, particularly potassium and uric acid levels at baseline and closely during treatment with VIVIMUSTA. Allopurinol has also been used during the beginning of bendamustine hydrochloride therapy. However, there may be an increased risk of severe skin toxicity when bendamustine hydrochloride and allopurinol are administered concomitantly [see Warnings and Precautions (5.6)].

5.6 Skin Reactions

Fatal and serious skin reactions have been reported with bendamustine hydrochloride treatment in clinical trials and postmarketing safety reports, including toxic skin reactions [Stevens-Johnson Syndrome (SJS), toxic epidermal necrolysis (TEN), and drug reaction with eosinophilia and systemic symptoms (DRESS)], bullous exanthema, and rash. Events occurred when bendamustine hydrochloride was given as a single agent and in combination with other anticancer agents or allopurinol. Where skin reactions occur, they may be progressive and increase in severity with further treatment.

Monitor patients with skin reactions closely. If skin reactions are severe or progressive, withhold or discontinue VIVIMUSTA.

5.7 Hepatotoxicity

Fatal and serious cases of liver injury have been reported with Bendamustine Hydrochloride Injection [see Adverse Reactions (6.1)]. Combination therapy, progressive disease or reactivation of hepatitis B were confounding factors in some patients [see Warnings and Precautions (5.2)]. Most cases were reported within the first three months of starting therapy.
Monitor liver chemistry tests prior to and during treatment with VIVIMUSTA.

5.8 Other Malignancies

Pre-malignant and malignant diseases have developed in patients who have been treated with bendamustine hydrochloride, including myelodysplastic syndrome, myeloproliferative disorders, acute myeloid leukemia, bronchial carcinoma, and non-melanoma skin cancer including basal cell carcinoma and squamous cell carcinoma [see Adverse Reactions (6.2)].
Monitor patients for the development of secondary malignancies. Perform dermatologic evaluations during and after treatment with VIVIMUSTA.

5.9 Extravasation Injury

Bendamustine hydrochloride extravasations have been reported in postmarketing resulting in hospitalizations from erythema, marked swelling, and pain.
Assure good venous access prior to starting VIVIMUSTA infusion and monitor the intravenous infusion site for redness, swelling, pain, infection, and necrosis during and after administration of VIVIMUSTA.

5.10 Embryo-Fetal Toxicity

Based on findings from animal reproduction studies and the drug's mechanism of action, VIVIMUSTA can cause fetal harm when administered to a pregnant woman. Single intraperitoneal doses of bendamustine (that approximated the maximum recommended human dose based on body surface area) to pregnant mice and rats during organogenesis caused adverse developmental outcomes, including an increase in resorptions, skeletal and visceral malformations, and decreased fetal body weights.
Advise pregnant women of the potential risk to a fetus. Advise females of reproductive potential to use an effective method of contraception during treatment with VIVIMUSTA and for 6 months after the last dose. Advise males with female partners of reproductive potential to use effective contraception during treatment with VIVIMUSTA and for 3 months after the last dose [see Use in Specific Populations (8.1, 8.3) and Clinical Pharmacology (12.1)].

6 ADVERSE REACTIONS

The following clinically significant adverse reactions are described elsewhere in the labelling:
• Myelosuppression [see Warnings and Precautions (5.1)]
• Infections [see Warnings and Precautions (5.2)]

• Progressive Multifocal Leukoencephalopathy [see Warnings and Precautions (5.3)]

• Anaphylaxis and Infusion-Related Reactions [see Warnings and Precautions (5.4)]
• Tumor Lysis Syndrome [see Warnings and Precautions (5.5)]
• Skin Reactions [see Warnings and Precautions (5.6)]
• Hepatotoxicity [see Warnings and Precautions (5.7)]
• Other Malignancies [see Warnings and Precautions (5.8)]
• Extravasation Injury [see Warnings and Precautions (5.9)]

6.1 Clinical Trials Experience

Because clinical trials are conducted under widely varying conditions, adverse reaction rates observed in the clinical trials of a drug cannot be directly compared to rates in the clinical trials of another drug and may not reflect the rates observed in practice.
Chronic Lymphocytic Leukemia (CLL)

The data described below reflect exposure to bendamustine hydrochloride in 153 patients. Bendamustine hydrochloride was studied in an active-controlled, randomized trial. The population was 45-77 years of age, 63% were male, 100% were White, and had treatment naïve CLL. All patients started the study at a dose of 100 mg/m2 intravenously over 30 minutes on Days 1 and 2 every 28 days.
Adverse reactions were reported according to NCI CTC v.2.0. In the randomized CLL clinical study, non-hematologic adverse reactions (any grade) in the bendamustine hydrochloride group that occurred with a frequency greater than 15% were pyrexia (24%), nausea (20%), and vomiting (16%).
Other adverse reactions seen frequently in one or more studies included asthenia, fatigue, malaise, and weakness; dry mouth; somnolence; cough; constipation; headache; mucosal inflammation and stomatitis.

Worsening hypertension was reported in 4 patients treated with bendamustine hydrochloride and in none treated with chlorambucil. Three of these 4 adverse reactions were described as a hypertensive crisis and were managed with oral medications and resolved.

The most frequent adverse reactions leading to study withdrawal for patients receiving bendamustine hydrochloride were hypersensitivity (2%) and pyrexia (1%).

Table 2 summarizes the adverse reactions that were reported in ≥ 5% of patients in either treatment group in the randomized CLL clinical study.

Table 2: Non-Hematologic Adverse Reactions that Occurred in at Least 5% of Patients Who Received Bendamustine Hydrochloride or Chlorambucil in the Randomized CLL Clinical Study

Adverse Reaction | Bendamustine Hydrochloride (N=153) |  | Chlorambucil (N=143)
Adverse Reaction | All Grades n (%) | Grade 3 or 4 n (%) | All Grades n (%) | Grade 3 or 4 n (%)
Total number of patients with at least 1 adverse reaction | 121 (79) | 52 (34) | 96 (67) | 25 (17)
Gastrointestinal disorders
Nausea | 31 (20) | 1 (<1) | 21 (15) | 1 (<1)
Vomiting | 24 (16) | 1 (<1) | 9 (6) | 0
Diarrhea | 14 (9) | 2 (1) | 5 (3) | 0
General disorders and administration site conditions
Pyrexia | 36 (24) | 6 (4) | 8 (6) | 2 (1)
Fatigue | 14 (9) | 2 (1) | 8 (6) | 0
Asthenia | 13 (8) | 0 | 6 (4) | 0
Chills | 9 (6) | 0 | 1 (<1) | 0
Immune system disorders
Hypersensitivity | 7 (5) | 2 (1) | 3 (2) | 0
Infections and infestations
Nasopharyngitis | 10 (7) | 0 | 12 (8) | 0
Infection | 9 (6) | 3 (2) | 1 (<1) | 1 (<1)
Herpes simplex | 5 (3) | 0 | 7 (5) | 0
Investigations
Weight decreased | 11 (7) | 0 | 5 (3) | 0
Metabolism and nutrition disorders
Hyperuricemia | 11 (7) | 3 (2) | 2 (1) | 0
Respiratory, thoracic and mediastinal disorders
Cough | 6 (4) | 1 (<1) | 7 (5) | 1 (<1)
Skin and subcutaneous tissue disorders
Rash | 12 (8) | 4 (3) | 7 (5) | 3 (2)
Pruritus | 8 (5) | 0 | 2 (1) | 0

Hematology laboratory abnormalities are described in Table 3. Red blood cell transfusions were administered to 20% of patients receiving bendamustine hydrochloride compared with 6% of patients receiving chlorambucil. Bilirubin elevation occurred in 34% of patients, some without associated significant elevations in AST and ALT. Grade 3 or 4 increased bilirubin occurred in 3% of patients. Increases in AST and ALT of Grade 3 or 4 were limited to 1% and 3% of patients, respectively. Patients treated with bendamustine hydrochloride may also have changes in their creatinine levels.
Table 3: Hematology Laboratory Abnormalities in Patients Who Received Bendamustine Hydrochloride or Chlorambucil in the Randomized CLL Clinical Study

Laboratory Abnormality | Bendamustine Hydrochloride (N=150) |  | Chlorambucil (N=141)
Laboratory Abnormality | All Grades n (%) | Grade 3 or 4 n (%) | All Grades n (%) | Grade 3 or 4 n (%)
Hemoglobin Decreased | 134 (89) | 20 (13) | 115 (82) | 12 (9)
Platelets Decreased | 116 (77) | 16 (11) | 110 (78) | 14 (10)
Neutrophils Decreased | 113 (75) | 65 (43) | 86 (61) | 30 (21)
Lymphocytes Decreased | 102 (68) | 70 (47) | 27 (19) | 6 (4)
Leukocytes Decreased | 92 (61) | 42 (28) | 26 (18) | 4 (3)

Non-Hodgkin Lymphoma (NHL)

The data described below reflect exposure to bendamustine hydrochloride in 176 patients with indolent B-cell NHL treated in two single-arm studies. The population was 31-84 years of age; 60% were male; 89% were White, 7% were Black, 3% were Hispanic, 1% were other, and <1% were Asian. These patients received bendamustine hydrochloride at a dose of 120 mg/m^2 intravenously on Days 1 and 2 for up to eight 21-day cycles.
In both studies, serious adverse reactions, were reported in 37% of patients receiving bendamustine hydrochloride. The most frequent serious adverse reactions occurring in ≥5% of patients were febrile neutropenia and pneumonia. Other important serious adverse reactions reported in clinical trials and/or postmarketing experience were acute renal failure, cardiac failure, hypersensitivity, skin reactions, pulmonary fibrosis, and myelodysplastic syndrome.
Serious adverse reactions reported in clinical trials included myelosuppression, infection, pneumonia, tumor lysis syndrome and infusion-related reactions [see Warningsand Precautions (5)]. Adverse reactions occurring less frequently but possibly related to bendamustine hydrochloride treatment were hemolysis, dysgeusia/taste disorder, atypical pneumonia, sepsis, herpes zoster, erythema, dermatitis, and skin necrosis.

The most common non-hematologic adverse reactions (≥30%) were nausea (75%), fatigue (57%), vomiting (40%), diarrhea (37%) and pyrexia (34%). The most common non-hematologic Grade 3 or 4 adverse reactions (≥5%) were fatigue (11%), febrile neutropenia (6%), and pneumonia, hypokalemia and dehydration, each reported in 5% of patients.
Non-hematologic adverse reactions are shown in Table 4.

Table 4: Non-Hematologic Adverse Reactions that Occurred in at Least 5% of Patients who Received Bendamustine Hydrochloride in the NHL Studies

 | Bendamustine Hydrochloride (N=176*)
Adverse Reaction | All Grades n(%) | Grade 3 or 4 n(%)
Total number of patients with at least 1 adverse reaction | 176 (100) | 94 (53)
Cardiac Disorders
Tachycardia | 13 (7) | 0
Gastrointestinal disorders
Nausea | 132 (75) | 7 (4)
Vomiting | 71 (40) | 5 (3)
Diarrhea | 65 (37) | 6 (3)
Constipation | 51 (29) | 1 (<1)
Stomatitis | 27 (15) | 1 (<1)
Abdominal pain | 22 (13) | 2 (1)
Dyspepsia | 20 (11) | 0
Gastroesophageal reflux disease | 18 (10) | 0
Dry mouth | 15 (9) | 1 (<1)
Abdominal pain upper | 8 (5) | 0
Abdominal distension | 8 (5) | 0
General disorders and administration site conditions
Fatigue | 101 (57) | 19 (11)
Pyrexia | 59 (34) | 3 (2)
Chills | 24 (14) | 0
Edema peripheral | 23 (13) | 1 (<1)
Asthenia | 19 (11) | 4 (2)
Chest pain | 11 (6) | 1 (<1)
Infusion site pain | 11 (6) | 0
Pain | 10 (6) | 0
Catheter site pain | 8 (5) | 0
Infections and infestations
Herpes zoster | 18 (10) | 5 (3)
Upper respiratory tract infection | 18 (10) | 0
Urinary tract infection | 17 (10) | 4 (2)
Sinusitis | 15 (9) | 0
Pneumonia | 14 (8) | 9 (5)
Febrile neutropenia | 11 (6) | 11 (6)
Oral candidiasis | 11 (6) | 2 (1)
Nasopharyngitis | 11 (6) | 0
Investigations
Weight decreased | 31 (18) | 3 (2)
Metabolism and nutrition disorders
Anorexia | 40 (23) | 3 (2)
Dehydration | 24 (14) | 8 (5)
Decreased appetite | 22 (13) | 1 (<1)
Hypokalemia | 15 (9) | 9 (5)
Musculoskeletal and connective tissue disorders
Back pain | 25 (14) | 5 (3)
Arthralgia | 11 (6) | 0
Pain in extremity | 8 (5) | 2 (1)
Bone pain | 8 (5) | 0
Nervous system disorders
Headache | 36 (21) | 0
Dizziness | 25 (14) | 0
Dysgeusia | 13 (7) | 0
Psychiatric disorder
Insomnia | 23 (13) | 0
Anxiety | 14 (8) | 1 (<1)
Depression | 10 (6) | 0
Respiratory, thoracic and mediastinal disorders
Cough | 38 (22) | 1 (<1)
Dyspnea | 28 (16) | 3 (2)
Pharyngolaryngeal pain | 14 (8) | 1 (<1)
Wheezing | 8 (5) | 0
Nasal congestion | 8 (5) | 0
Skin and subcutaneous tissue disorders
Rash | 28 (16) | 1 (<1)
Pruritus | 11 (6) | 0
Dry skin | 9 (5) | 0
Night sweats | 9 (5) | 0
Hyperhidrosis | 8 (5) | 0
Vascular disorders
Hypotension | 10 (6) | 2 (1)

*Patients may have reported more than 1 adverse reaction.

NOTE: Patients counted only once in each preferred term category and once in each body system category.

Hematologic toxicities, based on laboratory values and CTC grade, in patients with NHL treated in both single arm studies combined are described in Table 5. Clinically important chemistry laboratory values that were new or worsened from baseline and occurred in >1% of patients at grade 3 or 4, in patients with NHL who were treated in both single arm studies combined were hyperglycemia (3%), elevated creatinine (2%), hyponatremia (2%), and hypocalcemia (2%).
Table 5: Hematology Laboratory Abnormalities in Patients Who Received Bendamustine Hydrochloride in the NHL Studies

Hematology Variable | Bendamustine Hydrochloride
Hematology Variable | All Grades (%) | Grade 3 or 4 (%)
Lymphocytes Decreased | 99 | 94
Leukocytes Decreased | 94 | 56
Hemoglobin Decreased | 88 | 11
Neutrophils Decreased | 86 | 60
Platelets Decreased | 86 | 25

6.2 Postmarketing Experience

The following adverse reactions have been identified during postapproval use of bendamustine hydrochloride. Because these reactions are reported voluntarily from a population of uncertain size, it is not always possible to reliably estimate their frequency or establish a causal relationship to drug exposure.

Blood and lymphatic systems disorders: Pancytopenia.

Cardiovascular disorders: Atrial fibrillation, congestive heart failure (some fatal), myocardial infarction (some fatal), palpitation.

General disorders and administration site conditions: Injection site reactions (including phlebitis, pruritus, irritation, pain, swelling), infusion site reactions (including phlebitis, pruritus, irritation, pain, swelling).

Immune system disorders: Anaphylaxis.

Infections and infestations: Pneumocystis jiroveci pneumonia, progressive multifocal leukoencephalopathy (PML).

Renal and urinary disorders: Nephrogenic diabetes insipidus (NDI)

Respiratory, thoracic and mediastinal disorders: Pneumonitis.

Skin and subcutaneous tissue disorders: Stevens-Johnson syndrome (SJS), toxic epidermal necrolysis (TEN), drug reaction with eosinophilia and systemic symptoms (DRESS), and non-melanoma skin cancer (NMSC).

7 DRUG INTERACTIONS

7.1 Effect of Other Drugs on VIVIMUSTA

CYP1A2 Inhibitors
The coadministration of VIVIMUSTA with CYP1A2 inhibitors may increase bendamustine plasma concentrations and may result in increased incidence of adverse reactions with VIVIMUSTA [see Clinical Pharmacology (12.3)]. Consider alternative therapies that are not CYP1A2 inhibitors during treatment with VIVIMUSTA.

CYP1A2 Inducers
The coadministration of VIVIMUSTA with CYP1A2 inducers may decrease bendamustine plasma concentrations and may result in decreased efficacy of VIVIMUSTA [see Clinical Pharmacology (12.3)]. Consider alternative therapies that are not CYP1A2 inducers during treatment with VIVIMUSTA.

8 USE IN SPECIFIC POPULATIONS

8.1 Pregnancy

Risk Summary
In animal reproduction studies, intraperitoneal administration of bendamustine to pregnant mice and rats during organogenesis at doses 0.6 to 1.8 times the maximum recommended human dose (MRHD) resulted in embryo-fetal and/or infant mortality, structural abnormalities, and alterations to growth (see Data). There are no available data on bendamustine hydrochloride use in pregnant women to evaluate for a drug-associated risk of major birth defects, miscarriage or adverse maternal or fetal outcomes. Advise pregnant women of the potential risk to a fetus.
The estimated background risk of major birth defects and miscarriage for the indicated population is unknown. All pregnancies have a background risk of birth defect, loss, or other adverse outcomes. In the U.S. general population, the estimated background risk of major birth defects and miscarriage in clinically recognized pregnancies is 2% to 4% and 15% to 20%, respectively.
Data
Animal Data
Bendamustine hydrochloride was intraperitoneally administered once to mice from 210 mg/m^2 (approximately 1.8 times the MRHD) during organogenesis and caused an increase in resorptions, skeletal and visceral malformations (exencephaly, cleft palates, accessory rib, and spinal deformities) and decreased fetal body weights. This dose did not appear to be maternally toxic and lower doses were not evaluated. Repeat intraperitoneal administration of bendamustine hydrochloride in mice on gestation days 7 to 11 resulted in an increase in resorptions from 75 mg/m^2 (approximately 0.6 times the MRHD) and an increase in abnormalities from 112.5 mg/m^2 (approximately 0.9 times the MRHD), similar to those seen after a single intraperitoneal administration.
Bendamustine hydrochloride was intraperitoneally administered once to rats from 120 mg/m^2 (approximately the MRHD) on gestation days 4, 7, 9, 11, or 13 and caused embryo and fetal lethality as indicated by increased resorptions and a decrease in live fetuses. A significant increase in external (effect on tail, head, and herniation of external organs [exomphalos]) and internal (hydronephrosis and hydrocephalus) malformations were seen in dosed rats.

8.2 Lactation

Risk Summary
There are no data on the presence of bendamustine hydrochloride or its metabolites in either human or animal milk, the effects on the breastfed child, or the effects on milk production. Because of the potential for serious adverse reactions in the breastfed child, advise women not to breastfeed during treatment with VIVIMUSTA and for 1 week after the last dose.

8.3 Females and Males of Reproductive Potential

VIVIMUSTA can cause embryo-fetal harm when administered to a pregnant woman [see Use in Specific Populations (8.1)].

Pregnancy Testing
Pregnancy testing is recommended for females of reproductive potential prior to initiation of treatment with VIVIMUSTA.

Contraception

Females
Advise female patients of reproductive potential to use effective contraception during treatment with VIVIMUSTA and for 6 months after the last dose.
Males
Based on genotoxicity findings, advise males with female partners of reproductive potential to use effective contraception during treatment with VIVIMUSTA and for 3 months after the last dose [see Nonclinical Toxicology (13.1)].
Infertility
Based on findings from clinical studies, VIVIMUSTA may impair male fertility. Impaired spermatogenesis, azoospermia, and total germinal aplasia have been reported in male patients treated with alkylating agents, especially in combination with other drugs. In some instances spermatogenesis may return in patients in remission, but this may occur only several years after intensive chemotherapy has been discontinued. Advise patients of the potential risk to their reproductive capacities.
Based on findings from animal studies, VIVIMUSTA may impair male fertility due to an increase in morphologically abnormal spermatozoa. The long-term effects of VIVIMUSTA on male fertility, including the reversibility of adverse effects, have not been studied [see Nonclinical Toxicology (13.1)].

8.4 Pediatric Use

Safety and effectiveness in pediatric patients have not been established.
Safety, pharmacokinetics and efficacy were assessed in a single open-label trial (NCT01088984) in patients aged 1-19 years with relapsed or refractory acute leukemia, including 27 patients with acute lymphocytic leukemia (ALL) and 16 patients with acute myeloid leukemia (AML).
Bendamustine hydrochloride was administered as an intravenous infusion over 60 minutes on Days 1 and 2 of each 21-day cycle. There was no treatment response (CR+ CRp) in any patient. The safety profile in these patients was consistent with that seen in adults and no new safety signals were identified.
The pharmacokinetics of bendamustine in 43 patients, aged 1 to 19 years (median age of 10 years) were within range of values previously observed in adults given the same dose based on body surface area.

8.5 Geriatric Use

No overall differences in safety were observed between patients ≥65 years of age and younger patients. Efficacy was lower in patients 65 and over with CLL receiving bendamustine hydrochloride based upon an overall response rate of 47% for patients 65 and over and 70% for younger patients. Progression free survival was also longer in younger patients with CLL receiving bendamustine (19 months vs. 12 months). No overall differences in efficacy in patients with non-Hodgkin Lymphoma were observed between geriatric patients and younger patients.

8.6 Renal Impairment

Do not use VIVIMUSTA in patients with creatinine clearance (CLcr) less than 30 mL/min [see Clinical Pharmacology (12.3)].

8.7 Hepatic Impairment

Do not use VIVIMUSTA in patients with AST or ALT 2.5 to 10 times upper limit of normal (ULN) and total bilirubin 1.5 to 3 times ULN or total bilirubin greater than 3 times ULN [see Clinical Pharmacology (12.3)]

10 OVERDOSAGE

The intravenous lethal dose 50 (LD50) of bendamustine hydrochloride is 240 mg/m^2 in the mouse and rat. Toxicities included sedation, tremor, ataxia, convulsions and respiratory distress.
Across all clinical experience, the reported maximum single dose received was 280 mg/m^2. Three of four patients who received this dose showed ECG changes considered dose-limiting at 7 and 21 days post-dosing. These changes included QT prolongation (one patient), sinus tachycardia (one patient), ST and T wave deviations (two patients) and left anterior fascicular block (one patient). Cardiac enzymes and ejection fractions remained normal in all patients.
No specific antidote for bendamustine hydrochloride overdose is known. Management of overdosage should include general supportive measures, including monitoring of hematologic parameters and ECGs.

11 DESCRIPTION

Bendamustine hydrochloride is an alkylating agent. The chemical name of bendamustine hydrochloride monohydrate is 5-[Bis(2-chloroethyl)-amino]-1-methyl-1H-benzimidazole-2- butanoic acid hydrochloride monohydrate. Its empirical molecular formula is C16H21Cl2N3O2 ∙ HCl.H2O and the molecular weight is 412.74. Bendamustine hydrochloride monohydrate contains a mechlorethamine group and a benzimidazole heterocyclic ring with a butyric acid substituent, and has the following structural formula:

VIVIMUSTA (bendamustine hydrochloride injection) is intended for intravenous use after dilution with either 0.9% Sodium Chloride Injection, USP or 2.5% Dextrose/0.45% Sodium Chloride Injection, USP. It is supplied as a sterile, clear, and colorless to yellow solution in a clear glass multiple-dose vial. Each milliliter contains 25 mg of bendamustine hydrochloride equivalent to 22.7 mg of bendamustine, 5 mg of monothioglycerol, 39.45 mg (5% v/v) of absolute alcohol, and q.s. to 1 mL polyethylene glycol 400. Sodium hydroxide is used to adjust pH of polyethylene glycol 400.

12 CLINICAL PHARMACOLOGY

12.1 Mechanism of Action

Bendamustine is a bifunctional mechlorethamine derivative containing a purine-like benzimidazole ring. Mechlorethamine and its derivatives form electrophilic alkyl groups. These groups form covalent bonds with electron-rich nucleophilic moieties, resulting in interstrand DNA crosslinks. The bifunctional covalent linkage can lead to cell death via several pathways. Bendamustine is active against both quiescent and dividing cells. The exact mechanism of action of bendamustine remains unknown.

12.2 Pharmacodynamics

Based on the pharmacokinetics/pharmacodynamics analyses of data from adult patients with NHL, nausea increased with increasing bendamustine maximum concentrations (Cmax).
Cardiac Electrophysiology
The effect of bendamustine on the QTc interval was evaluated in 53 patients with indolent NHL and mantle cell lymphoma on Day 1 of Cycle 1 after administration of rituximab at 375 mg/m^2 intravenous infusion followed by a 30-minute intravenous infusion of bendamustine at 90 mg/m^2/day. No mean changes greater than 20 milliseconds were detected up to one hour post infusion. The potential for delayed effects on the QT interval after one hour was not evaluated.

12.3 Pharmacokinetics

Absorption

Following a single IV dose of bendamustine hydrochloride Cmax typically occurred at the end of infusion. The dose proportionality of bendamustine has not been studied.
Distribution
The protein binding of bendamustine ranged from 94-96% and was concentration independent from 1 to 50 μg/mL. The blood to plasma concentration ratios in human blood ranged from 0.84 to 0.86 over a concentration range of 10 to 100 μg/mL.
The mean steady-state volume of distribution (Vss) of bendamustine was approximately 20 to 25 L.
Elimination
After a single intravenous dose of 120 mg/m^2 of bendamustine over 1 hour, the intermediate half-life (t½) of the parent compound was approximately 40 minutes. The mean terminal elimination t½ of two active metabolites, γ-hydroxybendamustine (M3) and N desmethylbendamustine (M4) were approximately 3 hours and 30 minutes, respectively. Bendamustine clearance in humans was approximately 700 mL/min.
Metabolism
Bendamustine is extensively metabolized via hydrolytic, oxidative, and conjugative pathways. Bendamustine is primarily metabolized via hydrolysis to monohydroxy (HP1) and dihydroxy-bendamustine (HP2) metabolites with low cytotoxic activity in vitro. Two active minor metabolites, M3 and M4, are primarily formed via CYP1A2 in vitro. M3 and M4 concentrations of these metabolites in plasma are 1/10th and 1/100th that of the parent compound, respectively.
Excretion
Following intravenous infusion of radiolabeled bendamustine hydrochloride in patients with cancer, approximately 76% of the dose was recovered. Approximately 50% of the dose was recovered in the urine (3.3% unchanged) and approximately 25% of the dose was recovered in the feces. Less than 1% of the dose was recovered in the urine as M3 and M4, and less than 5% of the dose was recovered in the urine as HP2.
Specific Populations
No clinically meaningful effects on the pharmacokinetics of bendamustine were observed based on age (31 to 84 years), sex, mild to moderate renal impairment (CLcr ≥ 30 mL/min), or hepatic impairment with total bilirubin 1.5 < ULN and AST or ALT < 2.5 × ULN. The effects of severe renal impairment (CLcr < 30 mL/min), or hepatic impairment with total bilirubin 1.5 to 3 × ULN and AST or ALT 2.5 to 10 × ULN or total bilirubin > 3 × ULN on the pharmacokinetics of bendamustine is unknown.
Race/Ethnicity
Exposures in Japanese subjects (n=6) were 40% higher than non-Japanese subjects receiving the same dose. The clinical importance of this difference on the safety and efficacy of bendamustine hydrochloride in Japanese subjects has not been established.
Drug Interaction Studies

In Vitro Studies

Effect of Bendamustine Hydrochloride on CYP Substrates: Bendamustine hydrochloride did not inhibit CYP1A2, 2C9/10, 2D6, 2E1, or 3A4/5. Bendamustine hydrochloride did not induce metabolism of CYP1A2, CYP2A6, CYP2B6, CYP2C8, CYP2C9, CYP2C19, CYP2E1, or CYP3A4/5.

Effect of Transporters on Bendamustine Hydrochloride:Bendamustine hydrochloride is a substrate of P-glycoprotein and breast cancer resistance protein (BCRP).

13 NONCLINICAL TOXICOLOGY

13.1 Carcinogenesis & Mutagenesis & Impairment Of Fertility

Bendamustine was carcinogenic in mice. After intraperitoneal injections at 37.5 mg/m^2/day (the lowest dose tested, approximately 0.3 times the maximum recommended human dose [MRHD]) and 75 mg/m^2/day (approximately 0.6 times the MRHD) for 4 days, peritoneal sarcomas in female AB/jena mice were produced. Oral administration at 187.5 mg/m^2/day (the only dose tested, approximately 1.6 times the MRHD) for 4 days induced mammary carcinomas and pulmonary adenomas.
Bendamustine is a mutagen and clastogen. In a reverse bacterial mutation assay (Ames assay), bendamustine was shown to increase revertant frequency in the absence and presence of metabolic activation. Bendamustine was clastogenic in human lymphocytes in vitro, and in rat bone marrow cells in vivo (increase in micronucleated polychromatic erythrocytes) from 37.5 mg/m^2, (the lowest dose tested, approximately 0.3 times the MRHD).
Bendamustine induced morphologic abnormalities in spermatozoa in mice. Following tail vein injection of bendamustine at 120 mg/m^2 or a saline control on days 1 and 2 for a total of three weeks, the number of spermatozoa with morphologic abnormalities was 16% higher in the bendamustine-treated group as compared to the saline control group.

14 CLINICAL STUDIES

14.1 Chronic Lymphocytic Leukemia (CLL)

The efficacy of bendamustine hydrochloride was evaluated in an open-label, randomized, controlled multicenter trial comparing bendamustine hydrochloride to chlorambucil. The trial was conducted in 301 previously-untreated patients with Binet Stage B or C (Rai Stages I - IV) CLL requiring treatment. Need-to-treat criteria included hematopoietic insufficiency, B-symptoms, rapidly progressive disease or risk of complications from bulky lymphadenopathy. Patients with autoimmune hemolytic anemia or autoimmune thrombocytopenia, Richter’s syndrome, or transformation to prolymphocytic leukemia were excluded from the study. Patients were randomly assigned to receive either bendamustine hydrochloride 100 mg/m^2 intravenously over 30 minutes on Days 1 and 2 of each 28-day cycle or chlorambucil 0.8 mg/kg (Broca’s normal weight) orally on Days 1 and 15 of each 28-day cycle.
The patient populations in the bendamustine hydrochloride and chlorambucil treatment groups were balanced with regard to the following baseline characteristics: age (median 63 vs. 66 years), sex (63% vs. 61% male), Binet stage (71% vs. 69% Binet B), lymphadenopathy (79% vs. 82%), enlarged spleen (76% vs. 80%), enlarged liver (48% vs. 46%), hypercellular bone marrow (79% vs. 73%), “B” symptoms (51% vs. 53%), lymphocyte count (mean 65.7 x 10^9/L vs. 65.1 x 10^9/L), and serum lactate dehydrogenase concentration (mean 370.2 vs. 388.4 U/L). Ninety percent of patients in both treatment groups had immuno-phenotypic confirmation of CLL (CD5, CD23 and either CD19 or CD20 or both).
Efficacy endpoints of objective response rate and progression-free survival were calculated using a pre-specified algorithm based on NCI working group criteria for CLL. The results of this open-label randomized study demonstrated a higher rate of overall response and a longer progression-free survival for bendamustine hydrochloride compared to chlorambucil (see Table 6). Survival data are not mature.
Table 6: Efficacy Data for CLL

 | Bendamustine Hydrochloride (N=153) | Chlorambucil (N=148) | p-value
Response Rate n (%)
Overall response rate | 90 (59) | 38 (26) | <0.0001
(95% CI) | (51, 66.6) | (18.6, 32.7)
Complete response (CR)* | 13 (8) | 1 (<1)
Nodular partial response (nPR)** | 4 (3) | 0
Partial response (PR) † | 73 (48) | 37 (25)
Progression-Free Survival††
Median, months (95% CI) | 18 (11.7, 23.5) | 6 (5.6, 8.6)
Hazard ratio (95% CI) | 0.27 (0.17, 0.43) |  | <0.0001

CI = confidence interval

* CR was defined as peripheral lymphocyte count ≤ 4 x 109/L, neutrophils ≥ 1.5 x 109/L, platelets >100 x 109/L,
hemoglobin >110 g/L, without transfusions, absence of palpable hepatosplenomegaly, lymph nodes ≤ 1.5 cm,
< 30% lymphocytes without nodularity in at least a normocellular bone marrow and absence of “B” symptoms.
The clinical and laboratory criteria were required to be maintained for a period of at least 56 days.

** nPR was defined as described for CR with the exception that the bone marrow biopsy shows persistent nodules.
† PR was defined as ≥50% decrease in peripheral lymphocyte count from the pre-treatment baseline
value, and either ≥50% reduction in lymphadenopathy, or ≥50% reduction in the size of spleen or liver,
as well as one of the following hematologic improvements: neutrophils ≥ 1.5 x 109/L or 50% improvement over
baseline, platelets >100 x 109/L or 50% improvement over baseline, hemoglobin >110 g/L or 50% improvement
over baseline without transfusions, for a period of at least 56 days.
†† PFS was defined as time from randomization to progression or death from any cause.
Kaplan-Meier estimates of progression-free survival comparing bendamustine hydrochloride with chlorambucil are shown in Figure 1.

Figure 1. Progression-Free Survival

14.2 Non-Hodgkin Lymphoma (NHL)

The efficacy of bendamustine hydrochloride was evaluated in a single arm study of 100 patients with indolent B-cell NHL that had progressed during or within six months of treatment with rituximab or a rituximab-containing regimen. Patients were included if they relapsed within 6 months of either the first dose (monotherapy) or last dose (maintenance regimen or combination therapy) of rituximab. All patients received bendamustine hydrochloride 120 mg/m^2 intravenously on Days 1 and 2 of a 21-day treatment cycle for up to 8 cycles.
The median age was 60 years, 65% were male, and 95% had a baseline WHO performance status of 0 or 1. Major tumor subtypes were follicular lymphoma (62%), diffuse small lymphocytic lymphoma (21%), and marginal zone lymphoma (16%). Ninety-nine percent of patients had received previous chemotherapy, 91% of patients had received previous alkylator therapy, and 97% of patients had relapsed within 6 months of either the first dose (monotherapy) or last dose (maintenance regimen or combination therapy) of rituximab.
Efficacy was based on the assessments by a blinded independent review committee (IRC) and included overall response rate (complete response + complete response unconfirmed + partial response) and duration of response (DR) as summarized in Table 7.
Table 7: Efficacy Data for NHL*

 | Bendamustine Hydrochloride (N=100)
Response Rate (%)
Overall response rate (CR+CRu+PR) | 74
(95% CI) | (64.3, 82.3)
Complete response (CR) | 13
Complete response unconfirmed (CRu) | 4
Partial response (PR) | 57
Duration of Response (DR)
Median, months (95% CI) | 9.2 months (7.1, 10.8)

CI = confidence interval
*IRC assessment was based on modified International Working Group response criteria (IWG-RC). Modifications to IWG-RC specified that a persistently positive bone marrow in patients who met all other criteria for CR would be scored as PR. Bone marrow sample lengths were not required to be ≥20 mm.

15 REFERENCES

1. OSHA Hazardous Drugs. OSHA. https://www.osha.gov/hazardous-drugs

16 HOW SUPPLIED/STORAGE AND HANDLING

How Supplied
VIVIMUSTA (bendamustine hydrochloride injection) is a sterile clear, colorless to yellow solution for intravenous use supplied in individual cartons of multiple-dose vials providing 100 mg bendamustine hydrochloride per 4 mL.

100 mg/4 mL (25 mg/mL) NDC 24338-270-01
Safe Handling and Disposal

VIVIMUSTA (bendamustine hydrochloride injection) is a hazardous drug. Follow applicable special handling and disposal procedures^1. Care should be exercised in the handling and preparation of solutions prepared from VIVIMUSTA. The use of gloves and safety glasses is recommended to avoid exposure in case of breakage of the vial or other accidental spillage. If gloves come in contact with VIVIMUSTA prior to dilution, remove gloves and follow disposal procedures. If a solution of VIVIMUSTA (bendamustine hydrochloride injection) contacts the skin, wash the skin immediately and thoroughly with soap and water. If VIVIMUSTA (bendamustine hydrochloride injection) contacts the mucous membranes, flush thoroughly with water.
Storage

Store VIVIMUSTA (bendamustine hydrochloride injection) refrigerated at 2°C to 8°C (36°F to 46°F). Retain in original carton until time of use to protect from light.

17 PATIENT COUNSELING INFORMATION

Myelosuppression
Inform patients of the likelihood that bendamustine hydrochloride will cause a decrease in white blood cells, platelets, and red blood cells and the need for frequent monitoring of blood counts. Advise patients to report shortness of breath, significant fatigue, bleeding, fever, or other signs of infection [see Warnings and Precautions (5.1)].

Progressive Multifocal Leukoencephalopathy (PML)
Inform patients to immediately contact their healthcare provider if they experience confusion, memory loss, trouble thinking, difficulty talking or walking, vision loss or other neurological or cognitive symptoms [see Warnings and Precautions (5.3)].

Anaphylaxis and Infusion-Related Reactions
Inform patients of the possibility of serious or mild allergic reactions and to immediately report rash, facial swelling, or difficulty breathing during or soon after infusion [see Warnings and Precautions (5.4)].
Skin Reactions
Advise patients that a rash or itching may occur during treatment with VIVIMUSTA. Advise patients to immediately report severe or worsening rash or itching [see Warnings and Precautions (5.6)].
Hepatotoxicity
Inform patients of the possibility of developing liver function abnormalities and serious hepatic toxicity. Advise patients to immediately contact their healthcare provider if signs of liver failure occur, including jaundice, anorexia, bleeding or bruising [see Warnings and Precautions (5.7)].
Fatigue
Advise patients that VIVIMUSTA may cause tiredness and to avoid driving any vehicle or operating any dangerous tools or machinery if they experience this side effect [see Adverse Reactions (6.1)].
Nausea and Vomiting
Advise patients that VIVIMUSTA may cause nausea and/or vomiting. Patients should report nausea and vomiting so that symptomatic treatment may be provided [see Adverse Reactions (6.1)].
Diarrhea
Advise patients that VIVIMUSTA may cause diarrhea. Patients should report diarrhea to the healthcare provider so that symptomatic treatment may be provided [see Adverse Reactions (6.1)].

Non-melanoma Skin Cancer (NMSC)
Advise patients to undergo regular skin cancer screenings, and to report any suspicious skin changes to their healthcare provider [see Warnings and Precautions (5.8)].

Embryo-Fetal Toxicity
Advise pregnant women and females of reproductive potential of the potential risk to a fetus. Advise females to inform their healthcare provider of a known or suspected pregnancy [see Warnings and Precautions (5.10), Use in Specific Populations (8.1, 8.3), and Nonclinical Toxicology (13.1)].
Advise female patients of reproductive potential to use effective contraception during treatment with VIVIMUSTA and for 6 months after the last dose [see Use in Specific Populations (8.1, 8.3)].
Advise males with female partners of reproductive potential to use effective contraception during treatment with VIVIMUSTA and for 3 months after the last dose [see Use in Specific Populations (8.3) and Nonclinical Toxicology (13.1)].
Lactation
Advise females not to breastfeed during treatment with VIVIMUSTA and for 1 week after the last dose [see Use in Specific Populations (8.2)].

Infertility
Advise males of reproductive potential that VIVIMUSTA may impair fertility [see Use in Specific Populations (8.3)].

Manufactured for:
Azurity Pharmaceuticals, Inc.
Woburn, MA 01801 USA

Vivimusta® is a trademark of Azurity Pharmaceuticals, Inc.
Manufactured at:
Latina Pharma S.p.A.
04013 Sermoneta (LT), Italy.

Rev. MAR2025
VIV-PI-PE1-01

PACKAGE LABEL.PRINCIPAL DISPLAY PANEL

Principal Display Panel - Carton Label
NDC 24338-270-01
VIVIMUSTA® (bendamustine hydrochloride injection)

100 mg/4mL (25 mg/mL)

Principal Display Panel - Vial Label
NDC 24338-270-01

VIVIMUSTA® (bendamustine hydrochloride injection)

100 mg/4mL (25 mg/mL)